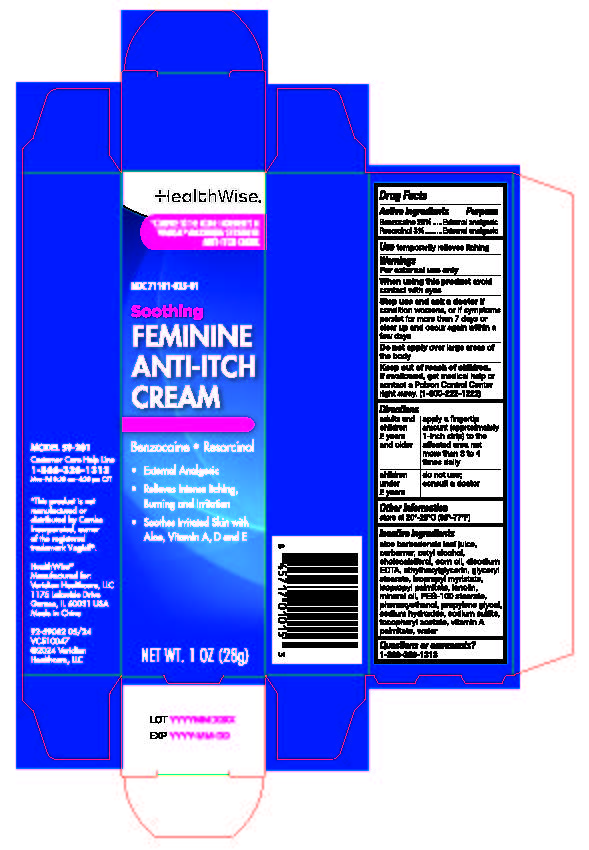 DRUG LABEL: HealthWise Feminine Anti-itch Cream
NDC: 71101-035 | Form: CREAM
Manufacturer: Veridian Healthcare
Category: otc | Type: HUMAN OTC DRUG LABEL
Date: 20240603

ACTIVE INGREDIENTS: BENZOCAINE 5.67 g/28 g; RESORCINOL 0.85 g/28 g
INACTIVE INGREDIENTS: ETHYLHEXYLGLYCERIN; ALOE VERA LEAF; EDETATE DISODIUM ANHYDROUS; CETYL ALCOHOL; CHOLECALCIFEROL; GLYCERYL 1-STEARATE; ISOPROPYL MYRISTATE; ISOPROPYL PALMITATE; CORN OIL; LANOLIN; CARBOMER HOMOPOLYMER TYPE A; MINERAL OIL; PEG-100 STEARATE; PROPYLENE GLYCOL; WATER; VITAMIN A PALMITATE; SODIUM HYDROXIDE; SODIUM SULFITE; .ALPHA.-TOCOPHEROL ACETATE; PHENOXYETHANOL

HealthWise Feminine Anti-itch Cream

Drug Facts Active ingredients

Benzocaine 20%
Resorcinol 3%

Purpose

External analgesic

Use

temporarily relieves itching

Warnings

For external use only

When using this product

avoid contact with the eyes

Stop use and ask a doctor if

condition worsens, or if symptoms persist for more than7 days or clear up and occur again within a few days

Do not apply Directions

Do not apply over large area of the body.

Other Information

store at 20° -25° C (68° -77° F)

Keep out of reach of children

If swallowed, get medical help or contact a Poison Control Center right away. (1-800-222-1222)

Directions

adults and children 2 years and older | apply a fingertip amount (approximately 1-inch strip) to the affected area not more than 3 to 4 times daily
children under 2 years | do not use; consult a doctor

Inactive Ingredients

aloe barbadensis leaf juice, carbomer, cetyl alcohol, cholecalciferol, corn oil, disodium EDTA, ethylhexylglycerin, glyceryl stearate, isopropyl myristate, isopropyl palmitate, lanolin, mineral oil, PEG-100 stearate, phenoxyethanol, propylene glycol sodium hydroxide, sodium sulfite, tocopheryl acetate, vitamin A palmitate, water

Questions or comments?

1-866-326-1313